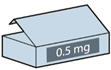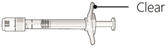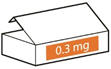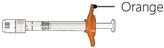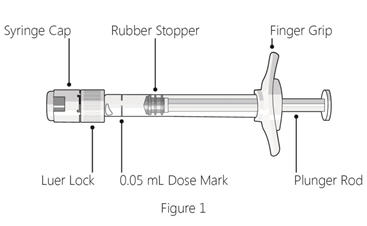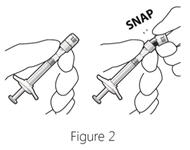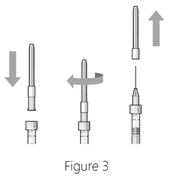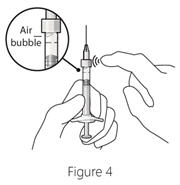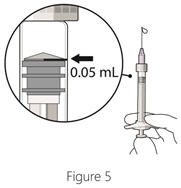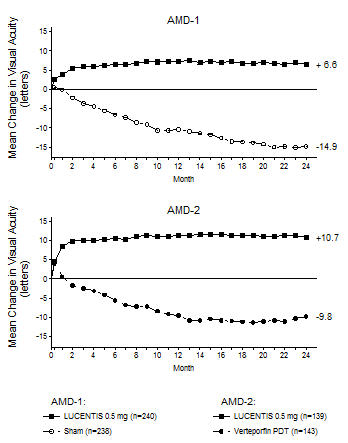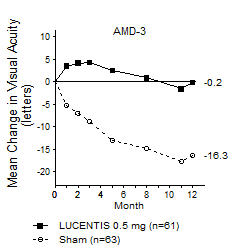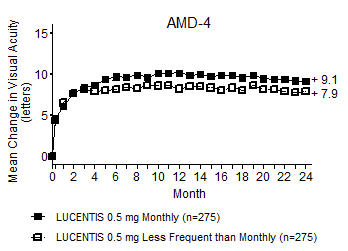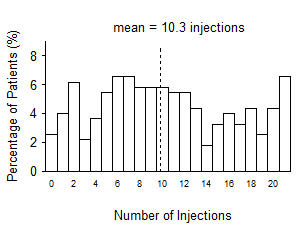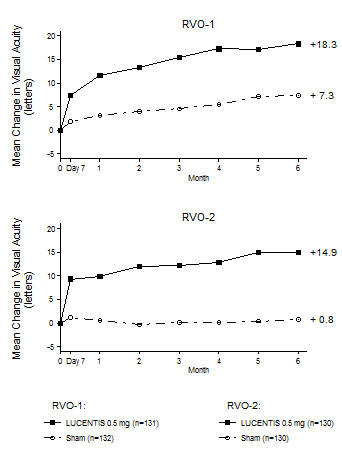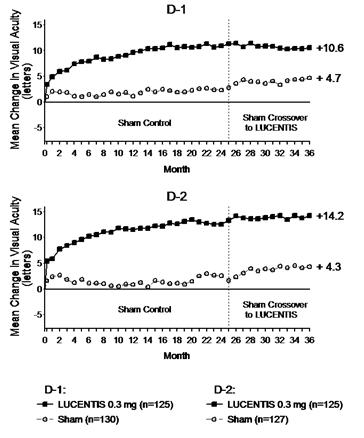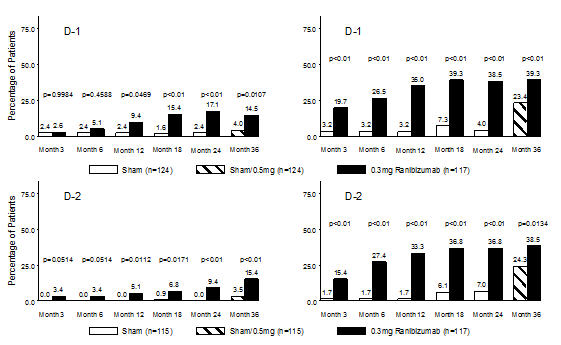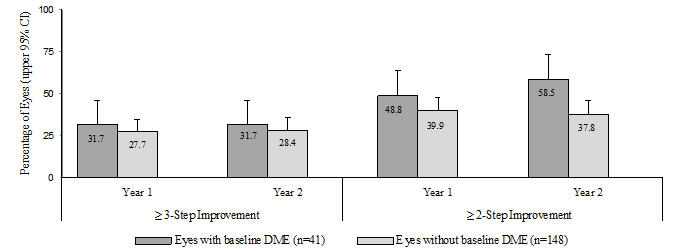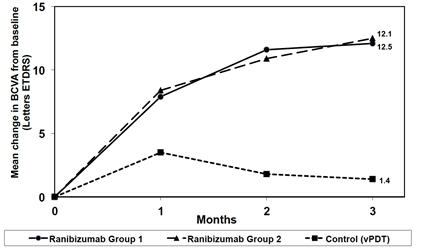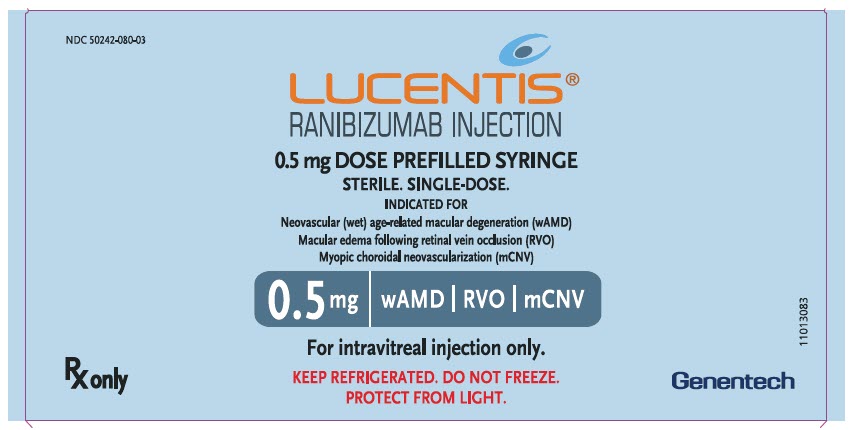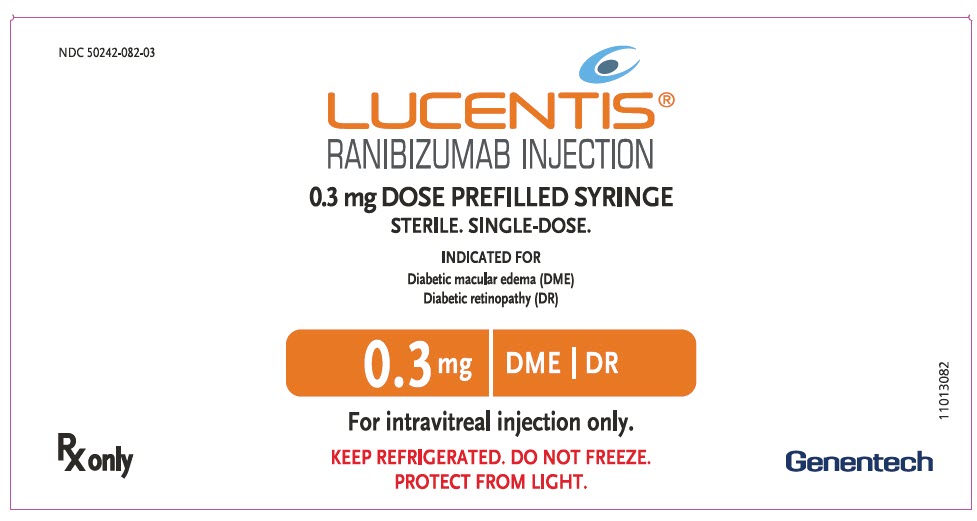 DRUG LABEL: LUCENTIS
NDC: 50242-080 | Form: INJECTION, SOLUTION
Manufacturer: Genentech, Inc.
Category: prescription | Type: HUMAN PRESCRIPTION DRUG LABEL
Date: 20251121

ACTIVE INGREDIENTS: RANIBIZUMAB 10 mg/1 mL
INACTIVE INGREDIENTS: HISTIDINE HYDROCHLORIDE 1.66 mg/1 mL; HISTIDINE 0.32 mg/1 mL; TREHALOSE DIHYDRATE 100 mg/1 mL; POLYSORBATE 20 0.1 mg/1 mL; WATER

HIGHLIGHTS OF PRESCRIBING INFORMATION

These highlights do not include all the information needed to use LUCENTIS safely and effectively. See full prescribing information for LUCENTIS.
LUCENTIS® (ranibizumab injection) for intravitreal injection
Initial U.S. Approval: 2006

RECENT MAJOR CHANGES

Dosage and Administration, General Dosing Information (2.1) | 8/2023
Dosage and Administration, Preparation for Administration (2.6) | 8/2023
Dosage and Administration, Administration (2.7) | 8/2023
Warnings and Precautions, Retinal Vasculitis with or without Occlusion (5.5) | 2/2024

1 INDICATIONS AND USAGE

LUCENTIS, a vascular endothelial growth factor (VEGF) inhibitor, is indicated for the treatment of patients with:

- Neovascular (Wet) Age-Related Macular Degeneration (AMD) (1.1)
- Macular Edema Following Retinal Vein Occlusion (RVO) (1.2)
- Diabetic Macular Edema (DME) (1.3)
- Diabetic Retinopathy (DR) (1.4)
- Myopic Choroidal Neovascularization (mCNV) (1.5)

2 DOSAGE AND ADMINISTRATION

For ophthalmic intravitreal injection only (2.1)

- Neovascular (Wet) Age-Related Macular Degeneration (AMD) (2.2):
  LUCENTIS 0.5 mg (0.05 mL of 10 mg/mL solution) is recommended to be administered by intravitreal injection once a month (approximately 28 days).
  - Although not as effective, patients may be treated with 3 monthly doses followed by less frequent dosing with regular assessment.
  - Although not as effective, patients may also be treated with one dose every 3 months after 4 monthly doses. Patients should be assessed regularly.
- Macular Edema Following Retinal Vein Occlusion (RVO) (2.3):
  LUCENTIS 0.5 mg (0.05 mL of 10 mg/mL solution) is recommended to be administered by intravitreal injection once a month (approximately 28 days).
- Diabetic Macular Edema (DME) and Diabetic Retinopathy (DR) (2.4):
  LUCENTIS 0.3 mg (0.05 mL of 6 mg/mL solution) is recommended to be administered by intravitreal injection once a month (approximately 28 days).
- Myopic Choroidal Neovascularization (mCNV) (2.5):
  LUCENTIS 0.5 mg (0.05 mL of 10 mg/mL solution) is recommended to be initially administered by intravitreal injection once a month (approximately 28 days) for up to three months. Patients may be retreated if needed.

3 DOSAGE FORMS AND STRENGTHS

- Single-dose prefilled syringe designed to provide 0.05 mL for intravitreal injections:
  - 10 mg/mL solution (LUCENTIS 0.5 mg) (3)
  - 6 mg/mL solution (LUCENTIS 0.3 mg) (3)

4 CONTRAINDICATIONS

- Ocular or periocular infections (4.1)
- Hypersensitivity (4.2)

5 WARNINGS AND PRECAUTIONS

- Endophthalmitis and retinal detachments may occur following intravitreal injections. Patients should be monitored following the injection (5.1).
- Increases in intraocular pressure (IOP) have been noted both pre- and post-intravitreal injection (5.2).
- There is a potential risk of arterial thromboembolic events following intravitreal use of VEGF inhibitors (5.3).
- Fatal events occurred more frequently in patients with DME and DR at baseline, who were treated monthly with LUCENTIS compared with control (5.4).

6 ADVERSE REACTIONS

- The most common adverse reactions (reported more frequently in LUCENTIS-treated subjects than control subjects) are conjunctival hemorrhage, eye pain, vitreous floaters, and increased IOP (6.2).

To report SUSPECTED ADVERSE REACTIONS, contact Genentech at 1-888-835-2555 or FDA at 1-800-FDA-1088 or www.fda.gov/medwatch.

FULL PRESCRIBING INFORMATION

1 INDICATIONS AND USAGE

LUCENTIS is indicated for the treatment of patients with:

2 DOSAGE AND ADMINISTRATION

2.1 General Dosing Information

FOR OPHTHALMIC INTRAVITREAL INJECTION.

2.2 Neovascular (Wet) Age-Related Macular Degeneration (AMD)

LUCENTIS 0.5 mg (0.05 mL of 10 mg/mL solution) is recommended to be administered by intravitreal injection once a month (approximately 28 days).

Although not as effective, patients may be treated with 3 monthly doses followed by less frequent dosing with regular assessment. In the 9 months after three initial monthly doses, less frequent dosing with 4-5 doses on average is expected to maintain visual acuity while monthly dosing may be expected to result in an additional average 1-2 letter gain. Patients should be assessed regularly [see Clinical Studies (14.1)].

Although not as effective, patients may also be treated with one dose every 3 months after 4 monthly doses. Compared with continued monthly dosing, dosing every 3 months over the next 9 months will lead to an approximate 5-letter (1-line) loss of visual acuity benefit, on average. Patients should be assessed regularly [see Clinical Studies (14.1)].

2.3 Macular Edema Following Retinal Vein Occlusion (RVO)

LUCENTIS 0.5 mg (0.05 mL of 10 mg/mL solution) is recommended to be administered by intravitreal injection once a month (approximately 28 days).

In Studies RVO-1 and RVO-2, patients received monthly injections of LUCENTIS for 6 months. In spite of being guided by optical coherence tomography and visual acuity re-treatment criteria, patients who were then not treated at Month 6 experienced on average, a loss of visual acuity at Month 7, whereas patients who were treated at Month 6 did not. Patients should be treated monthly [see Clinical Studies (14.2)].

2.4 Diabetic Macular Edema (DME) and Diabetic Retinopathy (DR)

LUCENTIS 0.3 mg (0.05 mL of 6 mg/mL solution) is recommended to be administered by intravitreal injection once a month (approximately 28 days).

2.5 Myopic Choroidal Neovascularization (mCNV)

LUCENTIS 0.5 mg (0.05 mL of 10 mg/mL LUCENTIS solution) is recommended to be initially administered by intravitreal injection once a month (approximately 28 days) for up to 3 months. Patients may be retreated if needed [see Clinical Studies (14.5)].

2.6 Preparation for Administration

Prefilled Syringe:

The prefilled syringe is sterile and is for single-dose only. Do not use the product if the packaging is damaged or has been tampered with.

To prepare LUCENTIS for intravitreal administration, please adhere to these instructions for use. Read all the instructions carefully before using the prefilled syringe.

The opening of the sealed tray and all subsequent steps should be done under aseptic conditions.

For the intravitreal injection, a 30-gauge × ½ inch sterile injection needle should be used (not provided).

Note: the dose must be set to 0.05 mL.

Device description

LUCENTIS prefilled syringes are available in 2 dose strengths:

- LUCENTIS 0.5 mg prefilled syringe with a CLEAR finger grip.

- LUCENTIS 0.3 mg prefilled syringe with an ORANGE finger grip.

Check the labels on the LUCENTIS carton, syringe tray and prefilled syringe to make sure you have the correct dose strength.

Step 1: Prepare

- Make sure that your pack contains a sterile prefilled syringe in a sealed tray.
- Peel the lid off the syringe tray and, using aseptic technique, remove the syringe.

Step 2: Inspect syringe

- LUCENTIS should be colorless to pale yellow.
- Do not use the prefilled syringe if:
  - the syringe cap is detached from the Luer lock.
  - the syringe is damaged.
  - particulates, cloudiness, or discoloration are visible.

Step 3: Remove syringe cap

- Snap off (do not turn or twist) the syringe cap (see Figure 2).

Step 4: Attach needle

- Attach a 30G × ½ inch sterile injection needle firmly onto the syringe by screwing it tightly onto the Luer lock (see Figure 3).
- Carefully remove the needle cap by pulling it straight off.

Note: Do not wipe the needle at any time.

Step 5: Dislodge air bubbles

- Hold the syringe with the needle pointing up.
- If there are any air bubbles, gently tap the syringe with your finger until the bubbles rise to the top (see Figure 4).

Step 6: Expel air and adjust drug dose

- Hold the syringe at eye level, and carefully push the plunger rod until the edge below the dome of the rubber stopper is aligned with the 0.05 mL dose mark (see Figure 5).

Note: The plunger rod is not attached to the rubber stopper – this is to prevent air being drawn into the syringe.

Step 7: Inject

- The injection procedure should be carried out under aseptic conditions.
- Insert the needle into the injection site.
- Inject slowly until rubber stopper reaches the bottom of the syringe to deliver the volume of 0.05 mL.
- After injection, do not recap the needle or detach it from the syringe. Dispose of the used syringe together with the needle in a sharps disposal container or in accordance with local requirements.

2.7 Administration

The intravitreal injection procedure should be carried out under controlled aseptic conditions, which include the use of sterile gloves, a sterile drape, and a sterile eyelid speculum (or equivalent). Adequate anesthesia and a broad-spectrum microbicide should be given prior to the injection.

Prior to and 30 minutes following the intravitreal injection, patients should be monitored for elevation in intraocular pressure using tonometry. Monitoring may also consist of a check for perfusion of the optic nerve head immediately after the injection [see Warnings and Precautions (5.2)]. Patients should also be monitored for and instructed to report any symptoms suggestive of endophthalmitis without delay following the injection [see Warnings and Precautions (5.1)].

Each prefilled syringe should only be used for the treatment of a single eye. If the contralateral eye requires treatment, a new prefilled syringe should be used and the sterile field, syringe, gloves, drapes, eyelid speculum, and injection needle should be changed before LUCENTIS is administered to the other eye.

No special dosage modification is required for any of the populations that have been studied (e.g., gender, elderly).

3 DOSAGE FORMS AND STRENGTHS

Single-dose prefilled syringe designed to provide 0.05 mL for intravitreal injection.

- Colorless to pale yellow 10 mg/mL solution (LUCENTIS 0.5 mg)
- Colorless to pale yellow 6 mg/mL solution (LUCENTIS 0.3 mg)

4 CONTRAINDICATIONS

4.1 Ocular or Periocular Infections

LUCENTIS is contraindicated in patients with ocular or periocular infections.

4.2 Hypersensitivity

LUCENTIS is contraindicated in patients with known hypersensitivity to ranibizumab or any of the excipients in LUCENTIS. Hypersensitivity reactions may manifest as severe intraocular inflammation.

5 WARNINGS AND PRECAUTIONS

5.1 Endophthalmitis and Retinal Detachments

Intravitreal injections, including those with LUCENTIS, have been associated with endophthalmitis and retinal detachments. Proper aseptic injection technique should always be used when administering LUCENTIS. In addition, patients should be monitored following the injection to permit early treatment should an infection occur [see Dosage and Administration (2.6, 2.7) and Patient Counseling Information (17)].

5.2 Increases in Intraocular Pressure

Increases in intraocular pressure have been noted both pre-injection and post-injection (at 60 minutes) while being treated with LUCENTIS. Monitor intraocular pressure prior to and following intravitreal injection with LUCENTIS and manage appropriately [see Dosage and Administration (2.7)].

5.3 Thromboembolic Events

Although there was a low rate of arterial thromboembolic events (ATEs) observed in the LUCENTIS clinical trials, there is a potential risk of ATEs following intravitreal use of VEGF inhibitors. Arterial thromboembolic events are defined as nonfatal stroke, nonfatal myocardial infarction, or vascular death (including deaths of unknown cause).

Neovascular (Wet) Age-Related Macular Degeneration

The ATE rate in the three controlled neovascular AMD studies (AMD-1, AMD-2, AMD-3) during the first year was 1.9% (17 of 874) in the combined group of patients treated with 0.3 mg or 0.5 mg LUCENTIS compared with 1.1% (5 of 441) in patients from the control arms [see Clinical Studies (14.1)]. In the second year of Studies AMD-1 and AMD-2, the ATE rate was 2.6% (19 of 721) in the combined group of LUCENTIS-treated patients compared with 2.9% (10 of 344) in patients from the control arms. In Study AMD-4, the ATE rates observed in the 0.5 mg arms during the first and second year were similar to rates observed in Studies AMD-1, AMD-2, and AMD-3.

In a pooled analysis of 2-year controlled studies [AMD-1, AMD-2, and a study of LUCENTIS used adjunctively with verteporfin photodynamic therapy (PDT)], the stroke rate (including both ischemic and hemorrhagic stroke) was 2.7% (13 of 484) in patients treated with 0.5 mg LUCENTIS compared to 1.1% (5 of 435) in patients in the control arms [odds ratio 2.2 (95% confidence interval (0.8-7.1)].

Macular Edema Following Retinal Vein Occlusion

The ATE rate in the two controlled RVO studies during the first 6 months was 0.8% in both the LUCENTIS and control arms of the studies (4 of 525 in the combined group of patients treated with 0.3 mg or 0.5 mg LUCENTIS and 2 of 260 in the control arms) [see Clinical Studies (14.2)]. The stroke rate was 0.2% (1 of 525) in the combined group of LUCENTIS-treated patients compared to 0.4% (1 of 260) in the control arms.

Diabetic Macular Edema and Diabetic Retinopathy

Safety data are derived from studies D-1 and D-2. All enrolled patients had DME and DR at baseline [see Clinical Studies (14.3, 14.4)].

In a pooled analysis of Studies D-1 and D-2 [see Clinical Studies (14.3)], the ATE rate at 2 years was 7.2% (18 of 250) with 0.5 mg LUCENTIS, 5.6% (14 of 250) with 0.3 mg LUCENTIS, and 5.2% (13 of 250) with control. The stroke rate at 2 years was 3.2% (8 of 250) with 0.5 mg LUCENTIS, 1.2% (3 of 250) with 0.3 mg LUCENTIS, and 1.6% (4 of 250) with control. At 3 years, the ATE rate was 10.4% (26 of 249) with 0.5 mg LUCENTIS and 10.8% (27 of 250) with 0.3 mg LUCENTIS; the stroke rate was 4.8% (12 of 249) with 0.5 mg LUCENTIS and 2.0% (5 of 250) with 0.3 mg LUCENTIS.

5.4 Fatal Events in Patients with Diabetic Macular Edema and Diabetic Retinopathy at Baseline

Diabetic Macular Edema and Diabetic Retinopathy

Safety data are derived from studies D-1 and D-2. All enrolled patients had DME and DR at baseline [see Clinical Studies (14.3, 14.4)].

A pooled analysis of Studies D-1 and D-2 [see Clinical Studies (14.3)], showed that fatalities in the first 2 years occurred in 4.4% (11 of 250) of patients treated with 0.5 mg LUCENTIS, in 2.8% (7 of 250) of patients treated with 0.3 mg LUCENTIS, and in 1.2% (3 of 250) of control patients. Over 3 years, fatalities occurred in 6.4% (16 of 249) of patients treated with 0.5 mg LUCENTIS and in 4.4% (11 of 250) of patients treated with 0.3 mg LUCENTIS. Although the rate of fatal events was low and included causes of death typical of patients with advanced diabetic complications, a potential relationship between these events and intravitreal use of VEGF inhibitors cannot be excluded.

5.5 Retinal Vasculitis with or without Occlusion

Retinal vasculitis with or without occlusion, typically in the presence of preexisting intraocular inflammation or post-treatment with other intravitreal agents, have been reported with the use of LUCENTIS. Discontinue treatment with LUCENTIS in patients who develop these events. Patients should be instructed to report any change in vision without delay [see Patient Counseling Information (17)].

6 ADVERSE REACTIONS

The following adverse reactions are discussed in greater detail in other sections of the label:

- Endophthalmitis and Retinal Detachments [see Warnings and Precautions (5.1)]
- Increases in Intraocular Pressure [see Warnings and Precautions (5.2)]
- Thromboembolic Events [see Warnings and Precautions (5.3)]
- Fatal Events in patients with DME and DR at baseline [see Warnings and Precautions (5.4)]

6.1 Injection Procedure

Serious adverse reactions related to the injection procedure have occurred in < 0.1% of intravitreal injections, including endophthalmitis [see Warnings and Precautions (5.1)], rhegmatogenous retinal detachment, and iatrogenic traumatic cataract.

6.2 Clinical Trials Experience

Because clinical trials are conducted under widely varying conditions, adverse reaction rates observed in the clinical trials of a drug cannot be directly compared to rates in the clinical trials of another drug and may not reflect the rates observed in practice.

The data below reflect exposure to 0.5 mg LUCENTIS in 440 patients with neovascular AMD in Studies AMD-1, AMD-2, and AMD-3; in 259 patients with macular edema following RVO. The data also reflect exposure to 0.3 mg LUCENTIS in 250 patients with DME and DR at baseline [see Clinical Studies (14)].

Safety data observed in 224 patients with mCNV, as well as Studies AMD-4 and D-3, were consistent with these results. On average, the rates and types of adverse reactions in patients were not significantly affected by dosing regimen.

Ocular Reactions

Table 1 shows frequently reported ocular adverse reactions in LUCENTIS-treated patients compared with the control group.

Table 1 Ocular Reactions in the DME and DR, AMD, and RVO Studies
 | DME and DR 2-year |  | AMD 2-year |  | AMD 1-year |  | RVO 6-month
Adverse Reaction | LUCENTIS 0.3 mg | Control | LUCENTIS 0.5 mg | Control | LUCENTIS 0.5 mg | Control | LUCENTIS 0.5 mg | Control
 | n=250 | n=250 | n=379 | n=379 | n=440 | n=441 | n=259 | n=260
Conjunctival hemorrhage | 47% | 32% | 74% | 60% | 64% | 50% | 48% | 37%
Eye pain | 17% | 13% | 35% | 30% | 26% | 20% | 17% | 12%
Vitreous floaters | 10% | 4% | 27% | 8% | 19% | 5% | 7% | 2%
Intraocular pressure increased | 18% | 7% | 24% | 7% | 17% | 5% | 7% | 2%
Vitreous detachment | 11% | 15% | 21% | 19% | 15% | 15% | 4% | 2%
Intraocular inflammation | 4% | 3% | 18% | 8% | 13% | 7% | 1% | 3%
Cataract | 28% | 32% | 17% | 14% | 11% | 9% | 2% | 2%
Foreign body sensation in eyes | 10% | 5% | 16% | 14% | 13% | 10% | 7% | 5%
Eye irritation | 8% | 5% | 15% | 15% | 13% | 12% | 7% | 6%
Lacrimation increased | 5% | 4% | 14% | 12% | 8% | 8% | 2% | 3%
Blepharitis | 3% | 2% | 12% | 8% | 8% | 5% | 0% | 1%
Dry eye | 5% | 3% | 12% | 7% | 7% | 7% | 3% | 3%
Visual disturbance or vision blurred | 8% | 4% | 18% | 15% | 13% | 10% | 5% | 3%
Eye pruritis | 4% | 4% | 12% | 11% | 9% | 7% | 1% | 2%
Ocular hyperemia | 9% | 9% | 11% | 8% | 7% | 4% | 5% | 3%
Retinal disorder | 2% | 2% | 10% | 7% | 8% | 4% | 2% | 1%
Maculopathy | 5% | 7% | 9% | 9% | 6% | 6% | 11% | 7%
Retinal degeneration | 1% | 0% | 8% | 6% | 5% | 3% | 1% | 0%
Ocular discomfort | 2% | 1% | 7% | 4% | 5% | 2% | 2% | 2%
Conjunctival hyperemia | 1% | 2% | 7% | 6% | 5% | 4% | 0% | 0%
Posterior capsule opacification | 4% | 3% | 7% | 4% | 2% | 2% | 0% | 1%
Injection site hemorrhage | 1% | 0% | 5% | 2% | 3% | 1% | 0% | 0%

Non-Ocular Reactions

Non-ocular adverse reactions with an incidence of ≥ 5% in patients receiving LUCENTIS for DR, DME, AMD, and/or RVO and which occurred at a ≥ 1% higher frequency in patients treated with LUCENTIS compared to control are shown in Table 2. Though less common, wound healing complications were also observed in some studies.

Table 2 Non-Ocular Reactions in the DME and DR, AMD, and RVO Studies
 | DME and DR 2-year |  | AMD 2-year |  | AMD 1-year |  | RVO 6-month
Adverse Reaction | LUCENTIS 0.3 mg | Control | LUCENTIS 0.5 mg | Control | LUCENTIS 0.5 mg | Control | LUCENTIS 0.5 mg | Control
 | n=250 | n=250 | n=379 | n=379 | n=440 | n=441 | n=259 | n=260
Nasopharyngitis | 12% | 6% | 16% | 13% | 8% | 9% | 5% | 4%
Anemia | 11% | 10% | 8% | 7% | 4% | 3% | 1% | 1%
Nausea | 10% | 9% | 9% | 6% | 5% | 5% | 1% | 2%
Cough | 9% | 4% | 9% | 8% | 5% | 4% | 1% | 2%
Constipation | 8% | 4% | 5% | 7% | 3% | 4% | 0% | 1%
Seasonal allergy | 8% | 4% | 4% | 4% | 2% | 2% | 0% | 2%
Hypercholesterolemia | 7% | 5% | 5% | 5% | 3% | 2% | 1% | 1%
Influenza | 7% | 3% | 7% | 5% | 3% | 2% | 3% | 2%
Renal failure | 7% | 6% | 1% | 1% | 0% | 0% | 0% | 0%
Upper respiratory tract infection | 7% | 7% | 9% | 8% | 5% | 5% | 2% | 2%
Gastroesophageal reflux disease | 6% | 4% | 4% | 6% | 3% | 4% | 1% | 0%
Headache | 6% | 8% | 12% | 9% | 6% | 5% | 3% | 3%
Edema peripheral | 6% | 4% | 3% | 5% | 2% | 3% | 0% | 1%
Renal failure chronic | 6% | 2% | 0% | 1% | 0% | 0% | 0% | 0%
Neuropathy peripheral | 5% | 3% | 1% | 1% | 1% | 0% | 0% | 0%
Sinusitis | 5% | 8% | 8% | 7% | 5% | 5% | 3% | 2%
Bronchitis | 4% | 4% | 11% | 9% | 6% | 5% | 0% | 2%
Atrial fibrillation | 3% | 3% | 5% | 4% | 2% | 2% | 1% | 0%
Arthralgia | 3% | 3% | 11% | 9% | 5% | 5% | 2% | 1%
Chronic obstructive pulmonary disease | 1% | 1% | 6% | 3% | 3% | 1% | 0% | 0%
Wound healing complications | 1% | 0% | 1% | 1% | 1% | 0% | 0% | 0%

6.3 Immunogenicity

As with all therapeutic proteins, there is the potential for an immune response in patients treated with LUCENTIS. The immunogenicity data reflect the percentage of patients whose test results were considered positive for antibodies to LUCENTIS in immunoassays and are highly dependent on the sensitivity and specificity of the assays.

The pre-treatment incidence of immunoreactivity to LUCENTIS was 0%-5% across treatment groups. After monthly dosing with LUCENTIS for 6 to 24 months, antibodies to LUCENTIS were detected in approximately 1%-9% of patients.

The clinical significance of immunoreactivity to LUCENTIS is unclear at this time. Among neovascular AMD patients with the highest levels of immunoreactivity, some were noted to have iritis or vitritis. Intraocular inflammation was not observed in patients with DME and DR at baseline, or RVO patients with the highest levels of immunoreactivity.

6.4 Postmarketing Experience

The following adverse reaction has been identified during post-approval use of LUCENTIS. Because this reaction was reported voluntarily from a population of uncertain size, it is not always possible to reliably estimate the frequency or establish a causal relationship to drug exposure.

- Ocular: Tear of retinal pigment epithelium among patients with neovascular AMD

7 DRUG INTERACTIONS

Drug interaction studies have not been conducted with LUCENTIS.

LUCENTIS intravitreal injection has been used adjunctively with PDT. Twelve of 105 (11%) patients with neovascular AMD developed serious intraocular inflammation; in 10 of the 12 patients, this occurred when LUCENTIS was administered 7 days (± 2 days) after PDT.

8 USE IN SPECIFIC POPULATIONS

8.1 Pregnancy

Risk Summary

There are no adequate and well-controlled studies of LUCENTIS administration in pregnant women.

Administration of ranibizumab to pregnant monkeys throughout the period of organogenesis resulted in a low incidence of skeletal abnormalities at intravitreal doses 13-times the predicted human exposure (based on maximal serum trough levels [Cmax]) after a single eye treatment at the recommended clinical dose. No skeletal abnormalities were observed at serum trough levels equivalent to the predicted human exposure after a single eye treatment at the recommended clinical dose [see Animal Data].

Animal reproduction studies are not always predictive of human response, and it is not known whether ranibizumab can cause fetal harm when administered to a pregnant woman. Based on the anti-VEGF mechanism of action for ranibizumab [see Clinical Pharmacology (12.1)], treatment with LUCENTIS may pose a risk to human embryofetal development.

LUCENTIS should be given to a pregnant woman only if clearly needed.

Data

Animal Data

An embryo-fetal developmental toxicity study was performed on pregnant cynomolgus monkeys. Pregnant animals received intravitreal injections of ranibizumab every 14 days starting on Day 20 of gestation, until Day 62 at doses of 0, 0.125, and 1 mg/eye. Skeletal abnormalities including incomplete and/or irregular ossification of bones in the skull, vertebral column, and hindlimbs and shortened supernumerary ribs were seen at a low incidence in fetuses from animals treated with 1 mg/eye of ranibizumab. The 1 mg/eye dose resulted in trough serum ranibizumab levels up to 13 times higher than predicted Cmax levels with single eye treatment in humans. No skeletal abnormalities were seen at the lower dose of 0.125 mg/eye, a dose which resulted in trough exposures equivalent to single eye treatment in humans. No effect on the weight or structure of the placenta, maternal toxicity, or embryotoxicity was observed.

8.2 Lactation

Risk Summary

There are no data available on the presence of ranibizumab in human milk, the effects of ranibizumab on the breastfed infant or the effects of ranibizumab on milk production/excretion.

Because many drugs are excreted in human milk, and because the potential for absorption and harm to infant growth and development exists, caution should be exercised when LUCENTIS is administered to a nursing woman.

The developmental and health benefits of breastfeeding should be considered along with the mother's clinical need for LUCENTIS and any potential adverse effects on the breastfed child from ranibizumab.

8.3 Females and Males of Reproductive Potential

Infertility

No studies on the effects of ranibizumab on fertility have been conducted and it is not known whether ranibizumab can affect reproduction capacity. Based on the anti-VEGF mechanism of action for ranibizumab, treatment with LUCENTIS may pose a risk to reproductive capacity.

8.4 Pediatric Use

The safety and effectiveness of LUCENTIS in pediatric patients have not been established.

8.5 Geriatric Use

In the clinical studies, approximately 76% (2449 of 3227) of patients randomized to treatment with LUCENTIS were ≥ 65 years of age and approximately 51% (1644 of 3227) were ≥ 75 years of age [see Clinical Studies (14)]. No notable differences in efficacy or safety were seen with increasing age in these studies. Age did not have a significant effect on systemic exposure.

10 OVERDOSAGE

More concentrated doses as high as 2 mg ranibizumab in 0.05 mL have been administered to patients. No additional unexpected adverse reactions were seen.

11 DESCRIPTION

LUCENTIS® (ranibizumab injection) is a recombinant humanized IgG1 kappa isotype monoclonal antibody fragment designed for intraocular use. Ranibizumab binds to and inhibits the biologic activity of human vascular endothelial growth factor A (VEGF-A). Ranibizumab, which lacks an Fc region, has a molecular weight of approximately 48 kilodaltons and is produced by an E. coli expression system in a nutrient medium containing the antibiotic tetracycline. Tetracycline is not detectable in the final product.

LUCENTIS is a sterile, colorless to pale yellow solution in a single-dose prefilled syringe. LUCENTIS is supplied as a preservative-free, sterile solution in a single-dose container designed to deliver 0.05 mL of 10 mg/mL LUCENTIS (0.5 mg dose prefilled syringe) or 6 mg/mL LUCENTIS (0.3 mg dose prefilled syringe) aqueous solution with 10 mM histidine HCl, 10% α,α-trehalose dihydrate, 0.01% polysorbate 20, pH 5.5.

12 CLINICAL PHARMACOLOGY

12.1 Mechanism of Action

Ranibizumab binds to the receptor binding site of active forms of VEGF-A, including the biologically active, cleaved form of this molecule, VEGF110. VEGF-A has been shown to cause neovascularization and leakage in models of ocular angiogenesis and vascular occlusion and is thought to contribute to pathophysiology of neovascular AMD, mCNV, DR, DME and macular edema following RVO. The binding of ranibizumab to VEGF-A prevents the interaction of VEGF-A with its receptors (VEGFR1 and VEGFR2) on the surface of endothelial cells, reducing endothelial cell proliferation, vascular leakage, and new blood vessel formation.

12.2 Pharmacodynamics

Increased retinal thickness (i.e., center point thickness (CPT) or central foveal thickness (CFT)), as assessed by optical coherence tomography (OCT) is associated with neovascular AMD, mCNV, macular edema following RVO, and DME. Leakage from choroidal neovascularization (CNV) as assessed by fluorescein angiography (FA) is associated with neovascular AMD and mCNV. Microvascular retinal changes and neovascularization, as assessed by color fundus photography, are associated with diabetic retinopathy.

Neovascular (Wet) Age-Related Macular Degeneration

In Study AMD-3, CPT was assessed by time domain (TD)-OCT in 118 of 184 patients. TD-OCT measurements were collected at baseline, Months 1, 2, 3, 5, 8, and 12. In patients treated with LUCENTIS, CPT decreased, on average, more than in the sham group from baseline through Month 12. CPT decreased by Month 1 and decreased further at Month 3, on average. In this study, CPT data did not provide information useful in influencing treatment decisions [see Clinical Studies (14.1)].

In Study AMD-4, CFT was assessed by spectral domain (SD)-OCT in all patients; on average, CFT reductions were observed beginning at Day 7 following the first LUCENTIS injection through Month 24. CFT data did not provide information capable of predicting final visual acuity results [see Clinical Studies (14.1)].

In patients treated with LUCENTIS, the area of CNV leakage, on average, decreased by Month 3 as assessed by FA. The area of CNV leakage for an individual patient was not correlated with visual acuity.

Macular Edema Following Retinal Vein Occlusion

On average, CPT reductions were observed in Studies RVO-1 and RVO-2 beginning at Day 7 following the first LUCENTIS injection through Month 6. CPT was not evaluated as a means to guide treatment decisions [see Clinical Studies (14.2)].

Diabetic Macular Edema

On average, CPT reductions were observed in Studies D-1 and D-2 beginning at Day 7 following the first LUCENTIS injection through Month 36. CPT data did not provide information useful in influencing treatment decisions [see Clinical Studies (14.3)].

Diabetic Retinopathy

Improvements from baseline in DR severity as assessed on fundus photography were observed in Studies D-1 and D-2 at Month 3 (first scheduled DR photographic assessment after randomization) through Month 36 [see Clinical Studies (14.4)].

Myopic Choroidal Neovascularization

On average CFT reductions were observed as early as Month 1, and were greater in the LUCENTIS groups compared to PDT [see Clinical Studies (14.5)].

12.3 Pharmacokinetics

In patients with neovascular AMD, following monthly intravitreal administration of 0.5 mg LUCENTIS, mean (±SD) maximum ranibizumab serum concentrations were 1.7 (± 1.1) ng/mL. These concentrations were below the concentration range of ranibizumab (11 to 27 ng/mL) that was necessary to inhibit the biological activity of VEGF-A by 50%, as measured in an in vitro cellular proliferation assay (based on human umbilical vein endothelial cells (HUVEC)). No significant change from baseline was observed in the mean plasma VEGF concentrations following three monthly 0.5 mg intravitreal injections. The maximum observed serum concentration was dose proportional over the dose range of 0.05 to 2 mg/eye. Serum ranibizumab concentrations in RVO and DME and DR patients were similar to those observed in neovascular AMD patients.

Based on a population pharmacokinetic analysis of patients with neovascular AMD, maximum serum concentrations are predicted to be reached at approximately 1 day after monthly intravitreal administration of LUCENTIS 0.5 mg/eye. Based on the disappearance of ranibizumab from serum, the estimated average vitreous elimination half-life was approximately 9 days. Steady-state minimum concentration is predicted to be 0.22 ng/mL with a monthly dosing regimen. In humans, serum ranibizumab concentrations are predicted to be approximately 90,000-fold lower than vitreal concentrations.

In pharmacokinetic covariate analyses, 48% (520/1091) of patients had renal impairment (35% mild, 11% moderate, and 2% severe). Because the increases in plasma ranibizumab exposures in these patients are not considered clinically significant, no dosage adjustment is needed based on renal impairment status.

13 NONCLINICAL TOXICOLOGY

13.1 Carcinogenesis, Mutagenesis, Impairment of Fertility

Animal studies have not been conducted to determine the carcinogenic potential of ranibizumab. Based on the anti-VEGF mechanism of action of ranibizumab, treatment with LUCENTIS may pose a risk to reproductive capacity [see Females and Males of Reproductive Potential (8.3)].

14 CLINICAL STUDIES

Unless otherwise noted, visual acuity was measured at a distance of 4 meters.

14.1 Neovascular (Wet) Age-Related Macular Degeneration (AMD)

The safety and efficacy of LUCENTIS were assessed in three randomized, double-masked, sham- or active-controlled studies in patients with neovascular AMD. A total of 1323 patients (LUCENTIS 879, control 444) were enrolled in the three studies.

Studies AMD-1 and AMD-2

In Study AMD-1, patients with minimally classic or occult (without classic) CNV lesions received monthly LUCENTIS 0.3 mg or 0.5 mg intravitreal injections or monthly sham injections. Data are available through Month 24. Patients treated with LUCENTIS in Study AMD-1 received a mean of 22 total treatments out of a possible 24 from Day 0 to Month 24.

In Study AMD-2, patients with predominantly classic CNV lesions received one of the following: 1) monthly LUCENTIS 0.3 mg intravitreal injections and sham PDT; 2) monthly LUCENTIS 0.5 mg intravitreal injections and sham PDT; or 3) sham intravitreal injections and active PDT. Sham PDT (or active PDT) was given with the initial LUCENTIS (or sham) intravitreal injection and every 3 months thereafter if FA showed persistence or recurrence of leakage. Data are available through Month 24. Patients treated with LUCENTIS in Study AMD-2 received a mean of 21 total treatments out of a possible 24 from Day 0 through Month 24.

In both studies, the primary efficacy endpoint was the proportion of patients who maintained vision, defined as losing fewer than 15 letters of visual acuity at 12 months compared with baseline. Almost all LUCENTIS-treated patients (approximately 95%) maintained their visual acuity. Among LUCENTIS-treated patients, 31% to 37% experienced a clinically significant improvement in vision, defined as gaining 15 or more letters at 12 months. The size of the lesion did not significantly affect the results. Detailed results are shown in Table 3, Table 4, and Figure 1 below.

Table 3 Visual Acuity Outcomes at Month 12 and Month 24 in Study AMD-1
Outcome Measure | Month | Sham n=229 | LUCENTIS 0.5 mg n=230 | Estimated Difference (95% CI) [Adjusted estimate based on the stratified model; p < 0.01]
Loss of <15 letters in visual acuity (%) | 12 | 60% | 91% | 30% (23%, 37%)
 | 24 | 56% | 89% | 33% (26%, 41%)
Gain of ≥15 letters in visual acuity (%) | 12 | 6% | 31% | 25% (18%, 31%)
 | 24 | 4% | 30% | 25% (18%, 31%)
Mean change in visual acuity (letters) (SD) | 12 | -11.0 (17.9) | +6.3 (14.1) | 17.1 (14.2, 20.0)
 | 24 | -15.0 (19.7) | +5.5 (15.9) | 20.1 (16.9, 23.4)

Table 4 Visual Acuity Outcomes at Month 12 and Month 24 in Study AMD-2
Outcome Measure | Month | PDT n=141 | LUCENTIS 0.5 mg n=139 | Estimated Difference (95% CI) [Adjusted estimate based on the stratified model; p < 0.01]
Loss of <15 letters in visual acuity (%) | 12 | 66% | 98% | 32% (24%, 40%)
 | 24 | 65% | 93% | 28% (19%, 37%)
Gain of ≥15 letters in visual acuity (%) | 12 | 11% | 37% | 26% (17%, 36%)
 | 24 | 9% | 37% | 29% (20%, 39%)
Mean change in visual acuity (letters) (SD) | 12 | -8.5 (17.8) | +11.0 (15.8) | 19.8 (15.9, 23.7)
 | 24 | -9.1 (18.7) | +10.9 (17.3) | 20 (16.0, 24.4)

Figure 1
Mean Change in Visual Acuity [Visual acuity was measured at a distance of 2 meters] from Baseline to Month 24 in Study AMD-1 and Study AMD-2

Patients in the group treated with LUCENTIS had minimal observable CNV lesion growth, on average. At Month 12, the mean change in the total area of the CNV lesion was 0.1-0.3 disc areas (DA) for LUCENTIS versus 2.3-2.6 DA for the control arms. At Month 24, the mean change in the total area of the CNV lesion was 0.3-0.4 DA for LUCENTIS versus 2.9-3.1 DA for the control arms.

Study AMD-3

Study AMD-3 was a randomized, double-masked, sham-controlled, 2-year study designed to assess the safety and efficacy of LUCENTIS in patients with neovascular AMD (with or without a classic CNV component). Data are available through Month 12. Patients received LUCENTIS 0.3 mg or 0.5 mg intravitreal injections or sham injections once a month for three consecutive doses, followed by a dose administered once every 3 months for 9 months. A total of 184 patients were enrolled in this study (LUCENTIS 0.3 mg, 60; LUCENTIS 0.5 mg, 61; sham, 63); 171 (93%) completed 12 months of this study. Patients treated with LUCENTIS in Study AMD-3 received a mean of six total treatments out of a possible 6 from Day 0 through Month 12.

In Study AMD-3, the primary efficacy endpoint was the mean change in visual acuity at 12 months compared with baseline (see Figure 2). After an initial increase in visual acuity (following monthly dosing), on average, patients dosed once every 3 months with LUCENTIS lost visual acuity, returning to baseline at Month 12. In Study AMD-3, almost all LUCENTIS-treated patients (90%) lost fewer than 15 letters of visual acuity at Month 12.

Figure 2
Mean Change in Visual Acuity from Baseline to Month 12 in Study AMD-3

Study AMD-4

Study AMD-4 was a randomized, double-masked, active treatment-controlled, two-year study designed to assess the safety and efficacy of LUCENTIS 0.5 mg administered monthly or less frequently than monthly in patients with neovascular AMD. Patients randomized to the LUCENTIS 0.5 mg less frequent dosing arm received three monthly doses followed by monthly assessments where patients were eligible to receive LUCENTIS injections guided by pre-specified re-treatment criteria. A total of 550 patients were enrolled in the two 0.5 mg treatment groups with 467 (85%) completing through Month 24. Data are available through Month 24.

Clinical results at Month 24 remain similar to that observed at Month 12.

From Month 3 through Month 24, visual acuity decreased by 0.3 letters in the 0.5 mg less frequent dosing arm and increased by 0.7 letters in the 0.5 mg monthly arm (see Figure 3). Over this 21-month period, patients in the 0.5 mg less frequent dosing and the 0.5 mg monthly arms averaged 10.3 and 18.5 injections, respectively. The distribution of injections received in the less frequent dosing arm is shown in Figure 4.

Figure 3
Mean Change in Visual Acuity from Baseline to Month 24 in Study AMD-4

Figure 4
Distribution of Injections from Month 3 to Month 24 in the Less Frequent Dosing Arm in Study AMD-4

14.2 Macular Edema Following Retinal Vein Occlusion (RVO)

The safety and efficacy of LUCENTIS were assessed in two randomized, double-masked, 1-year studies in patients with macular edema following RVO. Sham controlled data are available through Month 6. Patient age ranged from 20 to 91 years, with a mean age of 67 years. A total of 789 patients (LUCENTIS 0.3 mg, 266 patients; LUCENTIS 0.5 mg, 261 patients; sham, 262 patients) were enrolled, with 739 (94%) patients completing through Month 6. All patients completing Month 6 were eligible to receive LUCENTIS injections guided by pre-specified re-treatment criteria until the end of the studies at Month 12.

In Study RVO-1, patients with macular edema following branch or hemi-RVO, received monthly LUCENTIS 0.3 mg or 0.5 mg intravitreal injections or monthly sham injections for 6 months. All patients were eligible for macular focal/grid laser treatment beginning at Month 3 of the 6-month treatment period. Macular focal/grid laser treatment was given to 26 of 131 (20%) patients treated with 0.5 mg LUCENTIS and 71 of 132 (54%) patients treated with sham.

In Study RVO-2, patients with macular edema following central RVO received monthly LUCENTIS 0.3 mg or 0.5 mg intravitreal injections or monthly sham injections for 6 months.

At Month 6, after monthly treatment with 0.5 mg LUCENTIS, the following clinical results were observed:

Table 5 Visual Acuity Outcomes at Month 6 in Study RVO-1 and Study RVO-2
Outcome Measure | Study [RVO-1: Sham, n=131; LUCENTIS 0.5 mg, n=132 RVO-2: Sham, n=130; LUCENTIS 0.5 mg, n=130] | Sham | LUCENTIS 0.5 mg | Estimated Difference (95% CI) [Adjusted estimate based on stratified model; p < 0.01]
Gain of ≥15 letters in visual acuity (%) | RVO-1 | 29% | 61% | 31% (20%, 43%)
Gain of ≥15 letters in visual acuity (%) | RVO-2 | 17% | 48% | 30% (20%, 41%)

Figure 5
Mean Change in Visual Acuity from Baseline to Month 6 in Study RVO-1 and Study RVO-2

p < 0.01 for all time points

14.3 Diabetic Macular Edema (DME)

Efficacy and safety data of LUCENTIS are derived from studies D-1 and D-2 (See Section 14.4 Diabetic Retinopathy below). All enrolled patients had DR and DME at baseline.

The safety and efficacy of LUCENTIS were assessed in two randomized, double-masked, 3-year studies. The studies were sham-controlled through Month 24. Patient age ranged from 21 to 91 years, with a mean age of 62 years. A total of 759 patients (LUCENTIS 0.3 mg, 250 patients; LUCENTIS 0.5 mg, 252 patients; sham, 257 patients) were enrolled, with 582 (77%) completing through Month 36.

In Studies D-1 and D-2, patients received monthly LUCENTIS 0.3 mg or 0.5 mg intravitreal injections or monthly sham injections during the 24-month controlled treatment period. From Months 25 through 36, patients who previously received sham were eligible to receive monthly LUCENTIS 0.5 mg and patients originally randomized to monthly LUCENTIS 0.3 mg or 0.5 mg continued to receive their assigned dose. All patients were eligible for macular focal/grid laser treatment beginning at Month 3 of the 24-month treatment period or panretinal photocoagulation (PRP) as needed. Through Month 24, macular focal/grid laser treatment was administered in 94 of 250 (38%) patients treated with LUCENTIS 0.3 mg and 185 of 257 (72%) patients treated with sham; PRP was administered in 2 of 250 (1%) patients treated with LUCENTIS 0.3 mg and 30 of 257 (12%) patients treated with sham.

Compared to monthly LUCENTIS 0.3 mg, no additional benefit was observed with monthly treatment with LUCENTIS 0.5 mg. At Month 24, after monthly treatment with LUCENTIS 0.3 mg, the following clinical results were observed:

Table 6 Visual Acuity Outcomes at Month 24 in Study D-1 and D-2
Outcome Measure | Study [D-1: Sham, n=130; LUCENTIS 0.3 mg, n=125 D-2: Sham, n=127; LUCENTIS 0.3 mg, n=125] | Sham | LUCENTIS 0.3 mg | Estimated Difference (95% CI) [Adjusted estimate based on stratified model; p ≤ 0.01]
Gain of ≥15 letters in visual acuity (%) | D-1 | 12% | 34% | 21% (11%, 30%)
Gain of ≥15 letters in visual acuity (%) | D-2 | 18% | 45% | 24% (14%, 35%)
Loss of <15 letters in visual acuity (%) | D-1 | 92% | 98% | 7% (2%, 13%)
Loss of <15 letters in visual acuity (%) | D-2 | 90% | 98% | 8% (2%, 14%)
Mean change in visual acuity (letters) | D-1 | 2.3 | 10.9 | 8.5 (5.4, 11.5)
Mean change in visual acuity (letters) | D-2 | 2.6 | 12.5 | 9.6 (6.1, 13.0)

Figure 6
Mean Change in Visual Acuity from Baseline to Month 36 in Study D-1 and Study D-2

p < 0.01 for all time points comparing LUCENTIS 0.3 mg to sham through Month 24

Visual acuity outcomes observed at Month 24 in patients treated with LUCENTIS 0.3 mg were maintained with continued treatment through Month 36 in both DME studies. Patients in the sham arms who received LUCENTIS 0.5 mg beginning at Month 25 achieved lesser VA gains compared to patients who began treatment with LUCENTIS at the beginning of the studies.

In Studies D-1 and D-2, patients received monthly injections of LUCENTIS for 12 or 36 months, after which 500 patients opted to continue in the long-term follow-up study. Of 298 patients who had at least 12 months of follow-up from Month 36, 58 (19.5%) patients maintained vision with no further therapy. The remaining 202 patients were followed for less than 12 months.

14.4 Diabetic Retinopathy (DR)

Efficacy and safety data of LUCENTIS are derived from Studies D-1 and D-2 [see Clinical Studies (14.3)] and D-3. All enrolled patients in Studies D-1 and D-2 had DR and DME at baseline. Study D-3 enrolled DR patients both with and without DME at baseline.

Of the 759 patients enrolled in Studies D-1 and D-2, 746 patients had a baseline assessment of fundus photography. Patients had baseline Early Treatment Diabetic Retinopathy Study Diabetic Retinopathy Severity Scores (ETDRS-DRSS) ranging from 10 to 75. At baseline, 62% of patients had non-proliferative diabetic retinopathy (NPDR) (ETDRS-DRSS less than 60) and 31% had proliferative diabetic retinopathy (PDR) (ETDRS-DRSS greater than or equal to 60). The ETDRS-DRSS could not be graded in 5% of patients at baseline, and 2% of patients had absent or questionable DR at baseline. Approximately 20% of the overall population had prior PRP.

After monthly treatment with LUCENTIS 0.3 mg, the following clinical results were observed (Table 7; Figure 7):

Table 7 ≥3-Step and ≥2-Step Improvement at Month 24 in Study D-1 and Study D-2
Outcome Measure | Study [D-1: Sham, n=124; LUCENTIS 0.3 mg, n=117 D-2: Sham, n=115; LUCENTIS 0.3 mg, n=117] | Sham | LUCENTIS 0.3 mg | Estimated Difference (95% CI) [Adjusted estimate based on stratified model]
≥3-step improvement from baseline in ETDRS-DRSS [p < 0.05 for all time points comparing LUCENTIS 0.3 mg to sham from Month 12 through Month 24] | D-1 | 2% | 17% | 15% (7%, 22%)
≥3-step improvement from baseline in ETDRS-DRSS [p < 0.05 for all time points comparing LUCENTIS 0.3 mg to sham from Month 12 through Month 24] | D-2 | 0% | 9% | 9% (4%, 14%)
≥2-step improvement from baseline in ETDRS-DRSS [p < 0.05 for all time points comparing LUCENTIS 0.3 mg to sham from Month 3 through Month 24] | D-1 | 4% | 39% | 35% (26%, 44%)
≥2-step improvement from baseline in ETDRS-DRSS [p < 0.05 for all time points comparing LUCENTIS 0.3 mg to sham from Month 3 through Month 24] | D-2 | 7% | 37% | 31% (21%, 40%)

At Month 24, DR improvement by ≥3-steps in ETDRS-DRSS from baseline in subgroups examined (e.g., age, gender, race, baseline visual acuity, baseline HbA1c, prior DME therapy at baseline, baseline DR severity (NPDR, PDR)) were generally consistent with the results in the overall population.

The difference in the proportion of patients treated with LUCENTIS 0.3 mg compared to sham who achieved DR improvement based on the ETDRS-DRSS was observed as early as Month 3 for ≥2-step improvement or at Month 12 for ≥3-step improvement.

Figure 7
Proportion of Patients with ≥ 3-Step and ≥ 2-Step Improvement from Baseline in ETDRS Diabetic Retinopathy Severity Level over Time in Study D-1 and Study D-2

≥3-Step Improvement from Baseline Over Time

≥2-Step Improvement from Baseline Over Time

Study D-3 enrolled DR patients with and without DME; 88 (22%) eyes with baseline DME and 306 (78%) eyes without baseline DME and balanced across treatment groups. Study D-3 was a randomized, active-controlled study where patient age ranged from 20 to 83 with a mean age of 51 years. A total of 394 study eyes from 305 patients, including 89 who had both eyes randomized, were enrolled (LUCENTIS, 191 study eyes; pan-retinal photocoagulation; 203 study eyes). All eyes in the LUCENTIS group received a baseline 0.5 mg intravitreal injection followed by 3 monthly intravitreal injections, after which treatment was guided by pre-specified re-treatment criteria. Patients had baseline ETDRS-DRSS ranging from 20 to 85. At baseline, 11% of eyes had NPDR (ETDRS-DRSS less than 60), 50% had mild-to-moderate PDR (ETDRS-DRSS equal to 60, 61, or 65), and 37% had high-risk PDR (ETDRS-DRSS greater than or equal to 71).

An analysis of data from Study D-3 demonstrated that at Year 2 in the LUCENTIS group, 31.7% and 28.4% of eyes in the subgroups with baseline DME and without baseline DME, respectively, had ≥ 3-step improvement from baseline in ETDRS-DRSS.

Table 8 Proportion of Eyes with ≥ 3-Step and ≥ 2-Step Improvement from Baseline in ETDRS-DRSS at Year 2 in Study D-3
 | LUCENTIS group
Outcome Measure (in ETDRS-DRSS) | Eyes with Baseline DME n = 41 | Eyes without Baseline DME n = 148
≥ 3-step improvement from baseline 95% CI for percentage | 13 (31.7%) (17.5%, 46.0%) | 42 (28.4%) (21.1%, 35.6%)
≥ 2-step improvement from baseline 95% CI for percentage | 24 (58.5%) (43.5%, 73.6%) | 56 (37.8%) (30.0%, 45.7%)

Figure 8
Proportion of Eyes in the LUCENTIS group with ≥ 3-Step and ≥ 2-Step Improvement from Baseline in ETDRS-DRSS at Year 1 and Year 2 in Study D-3

14.5 Myopic Choroidal Neovascularization (mCNV)

The efficacy and safety data of LUCENTIS were assessed in a randomized, double-masked, active-controlled 3-month study in patients with mCNV. Patients age ranged from 18 to 87 years, with a mean age of 55 years. A total of 276 patients (222 patients in the LUCENTIS treated Groups I and II; 55 patients in the active control PDT group) were enrolled. Patients randomized to the LUCENTIS groups received injections guided by pre-specified re-treatment criteria. The retreatment criteria in Group I were vision stability guided, with the Best Corrected Visual Acuity (BCVA) at the current visit being assessed for changes compared with the two preceding monthly BCVA values. The retreatment criteria in Group II were disease activity guided, based on BCVA decrease from the previous visit that was attributable to intra- or sub-retinal fluid or active leakage secondary to mCNV as assessed by OCT and/or FA compared to the previous monthly visit.

Visual gains for the two LUCENTIS 0.5 mg treatment arms were superior to the active control arm. The mean change in BCVA from baseline at Month 3 was: +12.1 letters for Group I, +12.5 letters for Group II and +1.4 letters for the PDT group. (Figure 9; Table 9). Efficacy was comparable between Group I and Group II.

Table 9 Mean Change in Visual Acuity and Proportion of Patients who Gained ≥15 letters from Baseline at Month 3
Study Arms | Mean change in BCVA from baseline (Letters) |  | Proportion of patients who gained ≥15 letters from baseline
Study Arms | Mean (SD) | Estimated Difference (95% CI) [Adjusted estimates based on stratified models; p < 0.01] | Percent | Estimated Difference (95% CI)
Group I | 12.1 (10.2) | 10.9 (7.6, 14.3) | 37.1 | 22.6 (9.5, 35.7)
Group II | 12.5 (8.8) | 11.4 (8.3, 14.5) | 40.5 | 26.0 (13.1, 38.9)
Control (PDT) | 1.4 (12.2) |  | 14.5

Figure 9
Mean Change in Visual Acuity from Baseline to Month 3 in mCNV Study

The proportion of patients who gained ≥15 letters (ETDRS) by Month 3 was 37.1% and 40.5% for LUCENTIS Groups I and II, respectively and 14.5% for the PDT group. The mean number of injections between baseline and Month 3 was 2.5 and 1.8 for Groups I and II, respectively. 41% of patients received 1, 2 or 3 injections between baseline and Month 3 with no injections afterwards.

16 HOW SUPPLIED/STORAGE AND HANDLING

- Each LUCENTIS 0.5 mg carton (NDC 50242-080-03) contains a single-dose, prefilled syringe designed to deliver 0.05 mL of 10 mg/mL ranibizumab solution. The prefilled syringe has a non-retractable plunger stopper and a syringe cap consisting of a tamper-evident rigid seal with a rubber tip cap including a Luer lock adapter. The prefilled syringe has a plunger rod and a CLEAR finger grip. Each prefilled syringe is sterile and is packed in a sealed tray.
- Each LUCENTIS 0.3 mg carton (NDC 50242-082-03) contains a single-dose, prefilled syringe designed to deliver 0.05 mL of 6 mg/mL ranibizumab solution. The prefilled syringe has a non-retractable plunger stopper and a syringe cap consisting of a tamper-evident rigid seal with a rubber tip cap including a Luer lock adapter. The prefilled syringe has a plunger rod and an ORANGE finger grip. Each prefilled syringe is sterile and is packed in a sealed tray.

EACH CARTON IS FOR SINGLE-EYE USE ONLY.

STORAGE AND HANDLING

LUCENTIS should be refrigerated at 2º-8ºC (36º-46ºF). DO NOT FREEZE. Do not use beyond the date stamped on the label. Protect LUCENTIS prefilled syringes from light and store in the original carton until time of use. Do not open LUCENTIS prefilled syringe sealed tray until time of use.

17 PATIENT COUNSELING INFORMATION

Advise patients that in the days following LUCENTIS administration, patients are at risk of developing endophthalmitis and retinal vasculitis with or without occlusion. If the eye becomes red, sensitive to light, painful, or develops a change in vision, advise the patient to seek immediate care from an ophthalmologist [see Warnings and Precautions (5.1, 5.5)].

LUCENTIS® (ranibizumab injection)
Manufactured by: Genentech, Inc. A Member of the Roche Group 1 DNA Way South San Francisco, CA 94080-4990 | LUCENTIS® is a registered trademark of Genentech, Inc. ©2024 Genentech, Inc.

Representative sample of labeling (see the HOW SUPPLIED section for complete listing):

PRINCIPAL DISPLAY PANEL - 0.5 mg Syringe Carton

NDC 50242-080-03

LUCENTIS®
RANIBIZUMAB INJECTION

0.5 mg DOSE PREFILLED SYRINGE

STERILE. SINGLE-DOSE.

INDICATED FOR

Neovascular (wet) age-related macular degeneration (wAMD)
Macular edema following retinal vein occlusion (RVO)
Myopic choroidal neovascularization (mCNV)

0.5 mg
wAMD | RVO | mCNV

For intravitreal injection only.

Rx only

KEEP REFRIGERATED. DO NOT FREEZE.
PROTECT FROM LIGHT.

Genentech

11013083

PRINCIPAL DISPLAY PANEL - 0.3 mg Syringe Carton

NDC 50242-082-03

LUCENTIS®
RANIBIZUMAB INJECTION

0.3 mg DOSE PREFILLED SYRINGE

STERILE. SINGLE-DOSE.

INDICATED FOR

Diabetic macular edema (DME)
Diabetic retinopathy (DR)

0.3 mg
DME | DR

For intravitreal injection only.

Rx only

KEEP REFRIGERATED. DO NOT FREEZE.
PROTECT FROM LIGHT.

Genentech

11013082